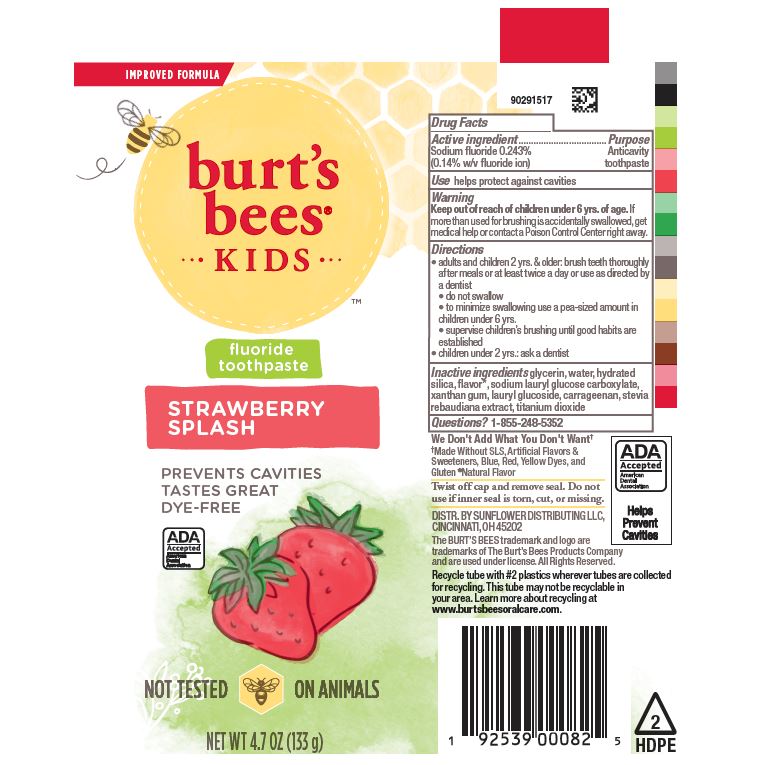 DRUG LABEL: Burts Bees Kids
NDC: 69423-819 | Form: PASTE, DENTIFRICE
Manufacturer: Procter & Gamble Manufacturing Company
Category: otc | Type: HUMAN OTC DRUG LABEL
Date: 20250806

ACTIVE INGREDIENTS: SODIUM FLUORIDE 1.3 mg/1 g
INACTIVE INGREDIENTS: SODIUM LAURYL GLYCOL CARBOXYLATE; CARRAGEENAN; TITANIUM DIOXIDE; XANTHAN GUM; WATER; HYDRATED SILICA; GLYCERIN; STEVIA REBAUDIANA WHOLE; SODIUM COCOYL GLUTAMATE; LAURYL GLUCOSIDE

Burt's Bees Kids Strawberry Splash

Drug Facts

Active ingredient

Sodium fluoride 0.243% (0.14% w/v fluoride ion)

Purpose

Anticavity toothpaste

Use

helps protect against cavities

Warnings

Keep out of reach of children under 6 yrs of age.If more than used for brushing is accidentally swallowed, get medical help or contact a Poison Control Center right away.

Directions

- adults and children 2 yrs. & older: brush teeth thoroughly after meals or at least twice a day or use as directed by a dentist
- do not swallow
- to minimize swallowing use a pea-sized amount in children under 6
- supervise children’s brushing until good habits are established
- children under 2 yrs.: ask a dentist

Inactive ingredients

glycerin, water, hydrated
silica, flavor*, sodium lauryl glucose carboxylate,
xanthan gum, lauryl glucoside, carrageenan, stevia
rebaudiana extract, titanium dioxide

Questions?

1-855-248-5352

*Natural Flavor

DISTR. BY SUNFLOWER DISTRIBUTING
LLC, CINCINNATI, OH 45202

PRINCIPAL DISPLAY PANEL - 119 g tube

IMPROVED FORMULA

burt's

bees®

KIDS

fluoride

toothpaste

STRARBERRY

SPLASH

PREVENTS CAVITIES
TASTES GREAT
DYE-FREE

ADA

Accepted

American

Dental

Association

NOT TESTED ON ANIMALS

NET WT 4.7 OZ (133 g)